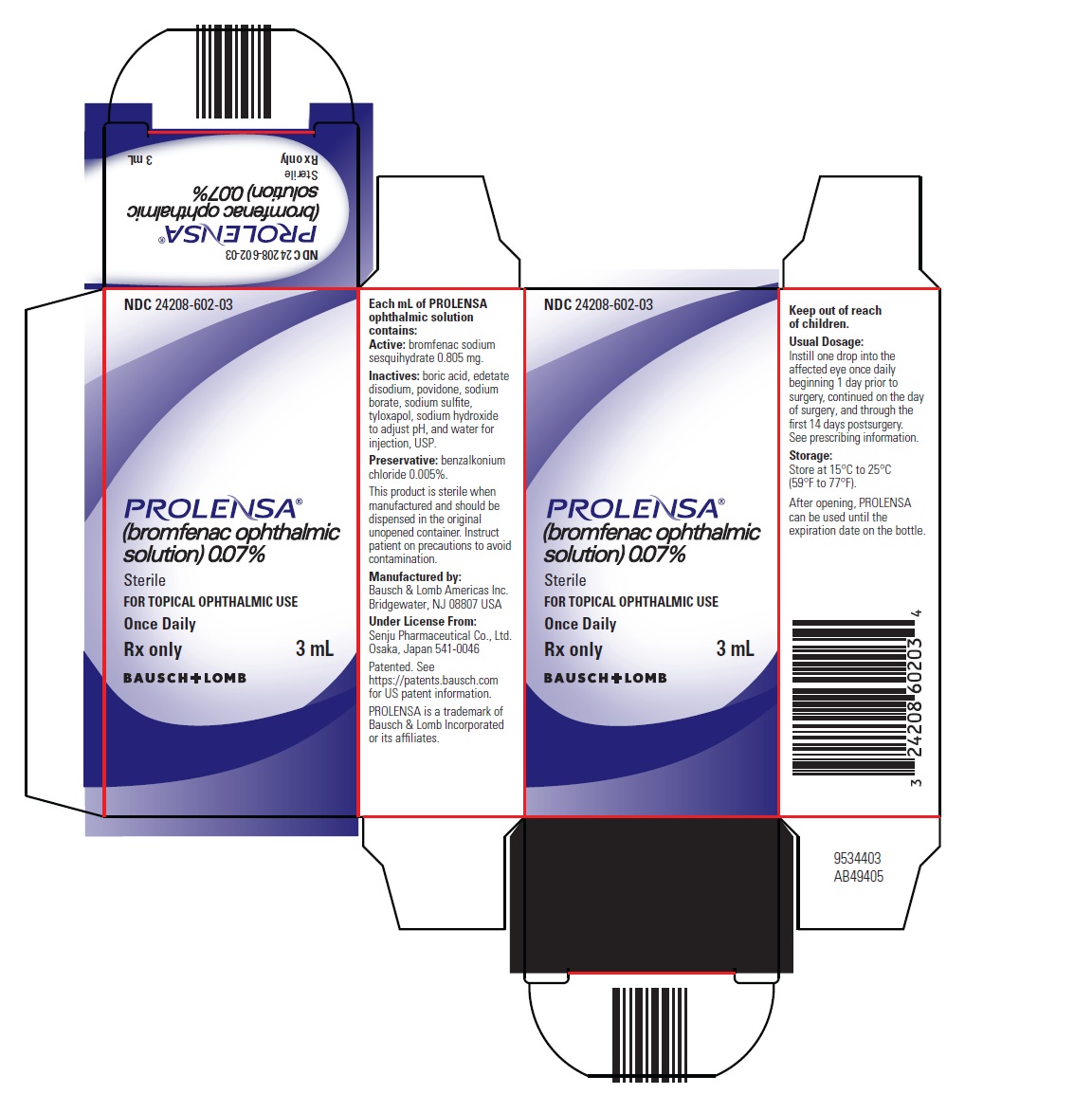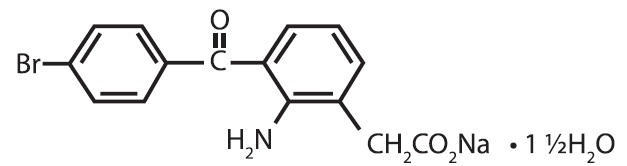 DRUG LABEL: Prolensa
NDC: 24208-602 | Form: SOLUTION/ DROPS
Manufacturer: Bausch & Lomb Incorporated
Category: prescription | Type: HUMAN PRESCRIPTION DRUG LABEL
Date: 20250606

ACTIVE INGREDIENTS: BROMFENAC SODIUM 0.7 mg/1 mL
INACTIVE INGREDIENTS: BENZALKONIUM CHLORIDE 0.05 mg/1 mL; BORIC ACID; EDETATE DISODIUM; POVIDONE, UNSPECIFIED; SODIUM BORATE; SODIUM SULFITE; TYLOXAPOL; SODIUM HYDROXIDE; WATER

HIGHLIGHTS OF PRESCRIBING INFORMATION

These highlights do not include all the information needed to use PROLENSA safely and effectively. See full prescribing information for PROLENSA.
PROLENSA®(bromfenac ophthalmic solution) 0.07%,
for topical ophthalmic use
Initial U.S. Approval: 1997

1 INDICATIONS AND USAGE

PROLENSA is a nonsteroidal anti-inflammatory drug (NSAID) indicated for the treatment of postoperative inflammation and reduction of ocular pain in patients who have undergone cataract surgery. (1)

2 DOSAGE AND ADMINISTRATION

Instill one drop into the affected eye once daily beginning 1 day prior to surgery, continued on the day of surgery, and through the first 14 days postsurgery. (2.1)

3 DOSAGE FORMS AND STRENGTHS

Ophthalmic solution: bromfenac 0.07% (3)

4 CONTRAINDICATIONS

None. (4)

5 WARNINGS AND PRECAUTIONS

• Sulfite Allergic Reactions (5.1)

• Slow or Delayed Healing (5.2)

• Potential for Cross-Sensitivity (5.3)

• Increased Bleeding Time (5.4)

• Keratitis and Corneal Reactions (5.5)

6 ADVERSE REACTIONS

The most commonly reported adverse reactions in 3% to 8% of patients were anterior chamber inflammation, foreign body sensation, eye pain, photophobia, and blurred vision. (6.1)

To report SUSPECTED ADVERSE REACTIONS, contact Bausch & Lomb Incorporated, at 1‑ 800-553-5340 or FDA at 1-800-FDA-1088 or www.fda.gov/medwatch.

FULL PRESCRIBING INFORMATION

1 INDICATIONS AND USAGE

PROLENSA®is indicated for the treatment of postoperative inflammation and reduction of ocular pain in patients who have undergone cataract surgery.

2 DOSAGE AND ADMINISTRATION

2.1 Recommended Dosage

Apply one drop to the affected eye once daily beginning 1 day prior to cataract surgery, continued on the day of surgery, and through the first 14 days of the postoperative period.

2.2 Use with Other Topical Ophthalmic Medications

PROLENSA may be administered in conjunction with other topical ophthalmic medications such as alpha agonists, beta-blockers, carbonic anhydrase inhibitors, cycloplegics, and mydriatics. Drops should be administered at least 5 minutes apart.

3 DOSAGE FORMS AND STRENGTHS

Ophthalmic solution: bromfenac 0.07%

4 CONTRAINDICATIONS

None.

5 WARNINGS AND PRECAUTIONS

5.1 Sulfite Allergic Reactions

PROLENSA contains sodium sulfite, a sulfite that may cause allergic-type reactions including anaphylactic symptoms and life-threatening or less severe asthmatic episodes in certain susceptible people. The overall prevalence of sulfite sensitivity in the general population is unknown and probably low. Sulfite sensitivity is seen more frequently in asthmatic than in non-asthmatic people.

5.2 Slow or Delayed Healing

All topical nonsteroidal anti-inflammatory drugs (NSAIDs), including bromfenac, may slow or delay healing. Topical corticosteroids are also known to slow or delay healing. Concomitant use of topical NSAIDs and topical steroids may increase the potential for healing problems.

5.3 Potential for Cross-Sensitivity

There is the potential for cross-sensitivity to acetylsalicylic acid, phenylacetic acid derivatives, and other NSAIDs, including bromfenac. Therefore, caution should be used when treating individuals who have previously exhibited sensitivities to these drugs.

5.4 Increased Bleeding Time

With some NSAIDs, including bromfenac, there exists the potential for increased bleeding time due to interference with platelet aggregation. There have been reports that ocularly applied NSAIDs may cause increased bleeding of ocular tissues (including hyphemas) in conjunction with ocular surgery.

It is recommended that PROLENSA ophthalmic solution be used with caution in patients with known bleeding tendencies or who are receiving other medications which may prolong bleeding time.

5.5 Keratitis and Corneal Reactions

Use of topical NSAIDs, including bromfenac, may result in keratitis. In some susceptible patients, continued use of topical NSAIDs may result in epithelial breakdown, corneal thinning, corneal erosion, corneal ulceration or corneal perforation. These events may be sight threatening. Patients with evidence of corneal epithelial breakdown should immediately discontinue use of topical NSAIDs, including bromfenac, and should be closely monitored for corneal health.

Postmarketing experience with topical NSAIDs suggests that patients with complicated ocular surgeries, corneal denervation, corneal epithelial defects, diabetes mellitus, ocular surface diseases (e.g., dry eye syndrome), rheumatoid arthritis, or repeat ocular surgeries within a short period of time may be at increased risk for corneal adverse events which may become sight threatening. Topical NSAIDs should be used with caution in these patients.

Postmarketing experience with topical NSAIDs also suggests that use more than 24 hours prior to surgery or use beyond 14 days postsurgery may increase patient risk for the occurrence and severity of corneal adverse events.

5.6 Risk of Contamination

Do not touch dropper tip to the eye, eyelids, or to any surface, as this may contaminate the contents. Replace the bottle cap after using.

5.7 Contact Lens Wear

PROLENSA should not be instilled while wearing contact lenses. Remove contact lenses prior to instillation of PROLENSA. The preservative in PROLENSA, benzalkonium chloride, may be absorbed by soft contact lenses. Lenses may be reinserted after 10 minutes following administration of PROLENSA.

6 ADVERSE REACTIONS

6.1 Clinical Trials Experience

Because clinical trials are conducted under widely varying conditions, adverse reaction rates observed in the clinical trials of a drug cannot be directly compared to rates in the clinical trials of another drug and may not reflect the rates observed in practice.

The most commonly reported adverse reactions following use of PROLENSA following cataract surgery include: anterior chamber inflammation, foreign body sensation, eye pain, photophobia, and vision blurred. These reactions were reported in 3% to 8% of patients.

8 USE IN SPECIFIC POPULATIONS

8.1 Pregnancy

Risk Summary

There are no available data on PROLENSA use in pregnant women to evaluate a drug-associated risk of major birth defects, miscarriage or other adverse maternal or fetal outcomes.

The systemic exposure to bromfenac following topical ocular administration is low [see Clinical Pharmacology (12.3)]. Consequently, the systemic exposure of a pregnant woman to bromfenac is expected to be minimal following topical ocular administration.

However, because of the known effects of prostaglandin biosynthesis-inhibiting drugs on the fetal cardiovascular system (closure of ductus arteriosus), the use of PROLENSA during late pregnancy should be avoided.

The estimated background risk of major birth defects and miscarriage for the indicated population is unknown. All pregnancies have a background risk of birth defect, loss or other adverse outcomes. In the U.S. general population, the estimated background risk of major birth defects and miscarriage in clinically recognized pregnancies is 2% to 4% and 15% to 20%, respectively.

Clinical Considerations

Premature closure of the ductus arteriosus in the fetus has occurred with third trimester use of oral and injectable NSAIDs. Measurable maternal and fetal plasma drug levels are available with oral and injectable routes of NSAID administration. The maternal plasma level of PROLENSA following ocular administration is unknown [see Clinical Pharmacology (12.3)].

Data

Animal Data

Embryo-fetal lethality and maternal toxicity were produced in rats and rabbits treated with bromfenac during the period of organogenesis at oral doses up to 0.9 mg/kg/day and 7.5 mg/kg/day, respectively. These doses corresponded to a Cmax 90- and 150- times the predicted Cmax at the recommended human ophthalmic dose (RHOD), respectively. In rats, bromfenac treatment caused delayed parturition at 0.3 mg/kg/day (30 times the predicted human Cmax at the RHOD), and caused dystocia, increased neonatal mortality, and reduced postnatal growth at 0.9 mg/kg/day (90 times the predicted human Cmax at the RHOD).

8.2 Lactation

There are no data on the presence of bromfenac in human milk, the effects on the breastfed infant, or the effects on milk production.

The systemic exposure of a breastfeeding woman to bromfenac is expected to be minimal following topical ocular administration, however, the possibility of harm to the breastfed infant cannot be ruled out.

The developmental and health benefits of breastfeeding should be considered, along with the mother’s clinical need for PROLENSA, and any potential adverse effects on the breastfed infant from PROLENSA or from the underlying maternal conditions.

8.4 Pediatric Use

The safety and effectiveness of PROLENSA have not been established in pediatric patients.

8.5 Geriatric Use

No overall differences in safety or effectiveness of PROLENSA have been observed between patients 70 years of age and older and younger adult patients.

11 DESCRIPTION

PROLENSA (bromfenac ophthalmic solution) 0.07% is a sterile, nonsteroidal anti-inflammatory drug (NSAID) for topical ophthalmic use. Each mL of PROLENSA contains 0.805 mg bromfenac sodium sesquihydrate (equivalent to 0.7 mg bromfenac free acid). The USAN name for bromfenac sodium sesquihydrate is bromfenac sodium. Bromfenac sodium is designated chemically as sodium [2-amino-3-(4-bromobenzoyl) phenyl] acetate sesquihydrate, with an empirical formula of C15H11BrNNaO3• 1½H2O. The chemical structure for bromfenac sodium sesquihydrate is:

Bromfenac sodium is a yellow to orange crystalline powder. The molecular weight of bromfenac sodium is 383.17. PROLENSA ophthalmic solution is supplied as a sterile aqueous 0.07% solution, with a pH of 7.8. The osmolality of PROLENSA ophthalmic solution is approximately 300 mOsmol/kg.

Each mL of PROLENSA ophthalmic solution contains:

ACTIVE:Each mL contains bromfenac sodium sesquihydrate 0.0805%, which is equivalent to bromfenac free acid 0.07%.

Inactives:boric acid, edetate disodium, povidone, sodium borate, sodium sulfite, tyloxapol, sodium hydroxide to adjust pH, and water for injection, USP.

Preservative:benzalkonium chloride 0.005%

12 CLINICAL PHARMACOLOGY

12.1 Mechanism of Action

Bromfenac is a nonsteroidal anti-inflammatory drug (NSAID) that has anti-inflammatory activity. The mechanism of its action is thought to be due to its ability to block prostaglandin synthesis by inhibiting cyclooxygenase (COX) 1 and 2. Prostaglandins have been shown in many animal models to be mediators of certain kinds of intraocular inflammation. In studies performed in animal eyes, prostaglandins have been shown to produce disruption of the blood-aqueous humor barrier, vasodilation, increased vascular permeability, leukocytosis, and increased intraocular pressure.

12.3 Pharmacokinetics

The plasma concentration of bromfenac following ocular administration of PROLENSA (bromfenac ophthalmic solution) 0.07% in humans is unknown. Based on the maximum proposed dose of one drop to each eye (0.035 mg) and PK information from other routes of administration, the systemic concentration of bromfenac is estimated to be below the limit of quantification (50 ng/mL) at steady-state in humans.

13 NONCLINICAL TOXICOLOGY

13.1 Carcinogenesis, Mutagenesis, Impairment of Fertility

Carcinogenesis

Long-term carcinogenicity studies in rats and mice given oral doses of bromfenac up to 0.6 mg/kg/day (systemic exposure 30 times the systemic exposure predicted from RHOD assuming the human systemic concentration is at the limit of quantification) and 5 mg/kg/day (340 times the predicted human systemic exposure), respectively, revealed no significant increases in tumor incidence.

Mutagenesis

Bromfenac did not show mutagenic potential in various mutagenicity studies, including the reverse mutation, chromosomal aberration, and micronucleus tests.

Impairment of Fertility

Bromfenac did not impair fertility when administered orally to male and female rats at doses up to 0.9 mg/kg/day and 0.3 mg/kg/day, respectively (systemic exposure 90 and 30 times the predicted human exposure, respectively).

14 CLINICAL STUDIES

14.1 Ocular Inflammation and Pain

Bromfenac 0.07% QD for the treatment of postoperative inflammation and reduction of ocular pain was evaluated in two multi-center, randomized, double-masked, parallel-group, and placebo (vehicle)-controlled studies. Patients undergoing cataract surgery self-administered bromfenac 0.07% or vehicle once daily, beginning 1 day prior to surgery, continuing on the morning of surgery and for 14 days after surgery. Complete clearance of ocular inflammation (0 cell and no flare) was assessed on Days 1, 3, 8, and 15 postsurgery using slit lamp biomicroscopy. The pain score was self-reported. The primary efficacy endpoint was the proportion of subjects who had complete clearance of ocular inflammation by Day 15. In the intent-to-treat analyses from both assessments, complete clearance at Day 8 and Day 15, bromfenac 0.07% was superior to vehicle as shown in the following table.

Proportion of Subjects with Cleared Ocular Inflammation (0 cell and no flare)
Study | Visit | Bromfenac 0.07% | Vehicle | Difference (%) (Asymptotic 95% CI)
Study 1 | At Day 8 | 27/112 (24.1%) | 7/108 (6.5%) | 17.6 (8.4, 26.8)
Study 1 | At Day 15 | 51/112 (45.5%) | 14/108 (13.0%) | 32.5 (21.4, 43.8)
Study 2 | At Day 8 | 33/110 (30.0%) | 14/110 (12.7%) | 17.3 (6.7, 27.9)
Study 2 | At Day 15 | 50/110 (45.5%) | 30/110 (27.3%) | 18.2 (5.7, 30.7)
Proportion of Subjects Who Were Pain Free
Study | Visit | Bromfenac 0.07% | Vehicle | Difference (%) (Asymptotic 95% CI)
Study 1 | At Day 1 | 91/112 (81.3%) | 47/108 (43.5%) | 37.7 (25.9, 49.6)
Study 2 | At Day 1 | 84/110 (76.4%) | 61/110 (55.5%) | 20.9 (8.7, 33.1)

16 HOW SUPPLIED/STORAGE AND HANDLING

PROLENSA®(bromfenac ophthalmic solution) 0.07% is supplied in a white LDPE plastic squeeze bottle with a 15 mm LDPE white dropper tip and 15 mm polypropylene gray cap as follows:

- NDC 24208-602-03 3 mL in a 7.5 mL bottle

Storage

Store at 15ºC to 25ºC (59ºF to 77ºF). After opening, PROLENSA can be used until the expiration date on the bottle.

17 PATIENT COUNSELING INFORMATION

Slow or Delayed Healing

Advise patients of the possibility that slow or delayed healing may occur while using NSAIDs.

Risk of Contamination

Advise patients to not touch dropper tip to the eye, eyelids, or to any surface, as this may contaminate the contents. Advise patients to replace bottle cap after using.

Contact Lens Wear

Advise patients to remove contact lenses prior to instillation of PROLENSA. The preservative in PROLENSA, benzalkonium chloride, may be absorbed by soft contact lenses. Lenses may be reinserted after 10 minutes following administration of PROLENSA.

Use with Other Topical Ophthalmic Medications

Advise patients that if more than one topical ophthalmic medication is being used, the medicines should be administered at least 5 minutes apart.

Manufactured by:
Bausch & Lomb Americas Inc.
Bridgewater, NJ 08807 USA
Under License From:
Senju Pharmaceutical Co., Ltd.
Osaka, Japan 541-0046
Patented. See https://patents.bausch.com for US patent information.
PROLENSA is a trademark of Bausch & Lomb Incorporated or its affiliates.

9306805 (Folded)
9306705 (Flat)

PACKAGE/LABEL PRINCIPAL DISPLAY PANEL

NDC24208-602-03

PROLENSA®
(bromfenac ophthalmic
solution) 0.07%

Sterile

FOR TOPICAL OPHTHALMIC USE

Once Daily

Rx only 3 mL

BAUSCH + LOMB

9534403
AB49405